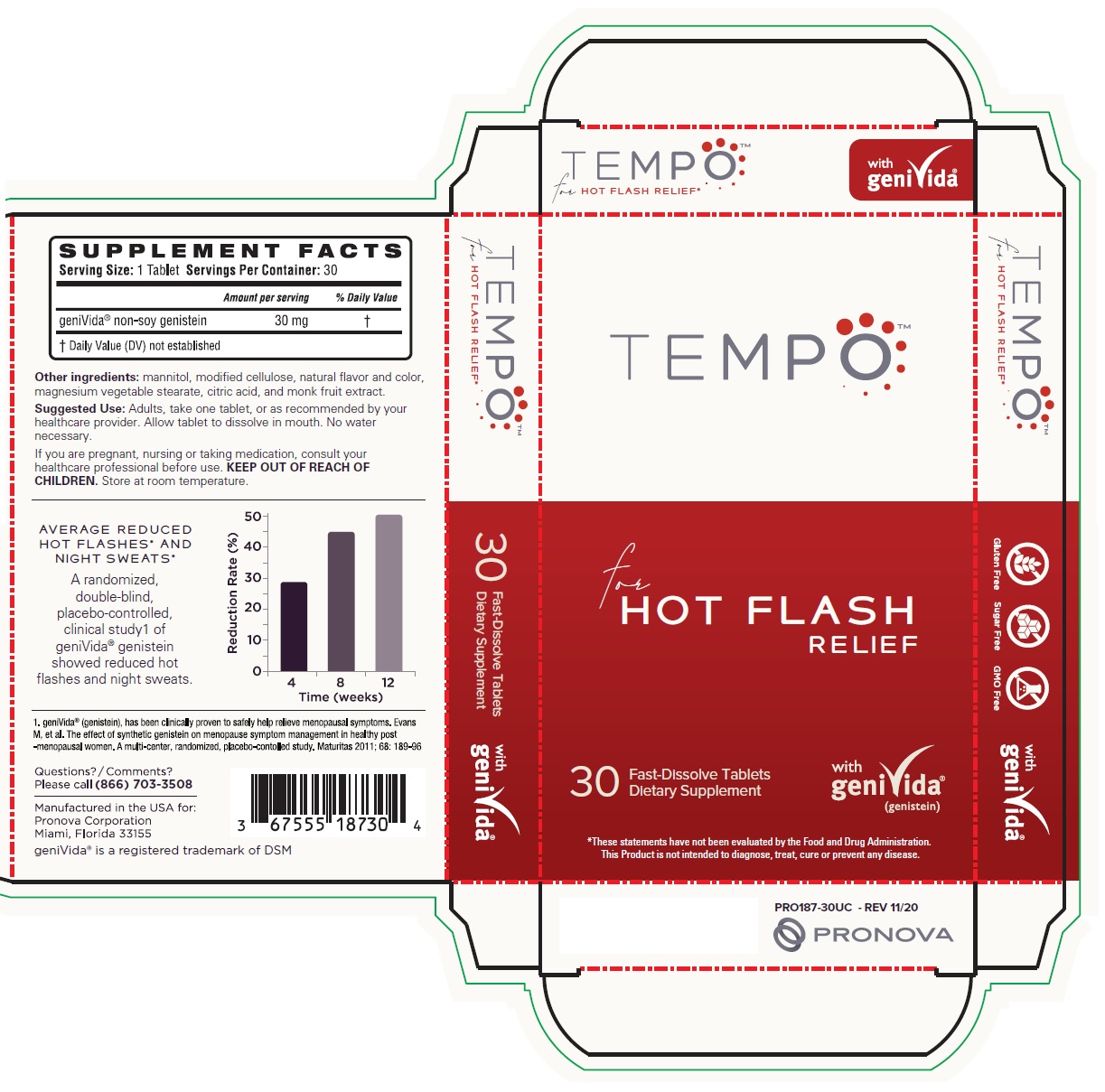 DRUG LABEL: TEMPO HOT FLASH RELIEF
NDC: 67555-187 | Form: TABLET, ORALLY DISINTEGRATING
Manufacturer: Pronova Corporation
Category: other | Type: DIETARY SUPPLEMENT
Date: 20230424

ACTIVE INGREDIENTS: GENISTEIN 30 mg/1 1
INACTIVE INGREDIENTS: MANNITOL; HYDROXYPROPYL CELLULOSE, UNSPECIFIED; MAGNESIUM STEARATE; CITRIC ACID MONOHYDRATE; SIRAITIA GROSVENORII FRUIT

TEMPOTM for HOT FLASH RELIEF

STATEMENT OF IDENTITY

SUPPLEMENT FACTS
Serving Size: 1 Tablet Servings Per Container: 30

Amount per serving

% Daily Value

geniVida® non-soy genistein

30 mg

†

† Daily Value (DV) not established

Other ingredients: mannitol, modified cellulose, natural flavor and color, magnesium vegetable stearate, citric acid, and monk fruit extract.

DOSAGE AND ADMINISTRATION

Suggested Use: Adults, take one tablet, or as recommended by your healthcare provider. Allow tablet to dissolve in mouth. No water necessary.

WARNINGS

If you are pregnant, nursing or taking medication, consult your healthcare professional before use. KEEP OUT OF REACH OF CHILDREN. Store at room temperature.

HEALTH CLAIM

Fast-Dissolve Tablets

Dietary Supplement

with geniVida® (genistein)

*These statements have not been evaluated by the Food and Drug Administration.
This product is not intended to diagnose, treat, cure or prevent any disease.

AVERAGE REDUCED HOT FLASHES* AND NIGHT SWEATS*

A randomized, double-blind, placebo-controlled, clinical study^1 of geniVida® genistein showed reduced hot flashes and night sweats.

^1. geniVida® (genistein), has been clinically proven to safely help relieve menopausal symptoms. Evans M, et al. The effect of synthetic genistein on menopause symptom management in healthy post-menopausal women. A multi-center, randomized, placebo-controlled study. Maturitas 2011;68: 189-96

Questions?/Comments?
Please call (866) 703-3508

Manufactured in the USA for:
Pronova Corporation
Miami, Florida 33155
geniVida® is a registered trademark of DSM

Gluten Free
Sugar Free
GMO Free

PRO187-30UC - REV 11/20